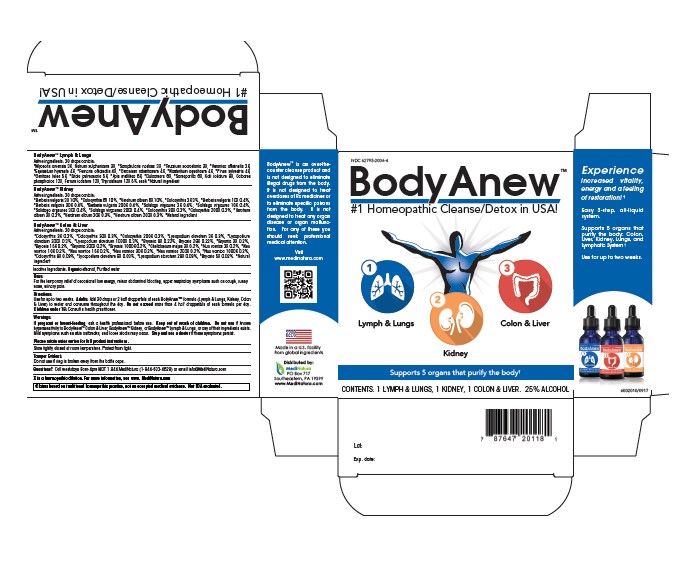 DRUG LABEL: BodyAnew
NDC: 62795-2004 | Form: KIT | Route: ORAL
Manufacturer: MediNatura Inc
Category: homeopathic | Type: HUMAN OTC DRUG LABEL
Date: 20230822

ACTIVE INGREDIENTS: BRYONIA ALBA ROOT 3 [hp_X]/50 mL; CHELIDONIUM MAJUS 3 [hp_X]/50 mL; CITRULLUS COLOCYNTHIS FRUIT PULP 3 [hp_X]/50 mL; LYCOPODIUM CLAVATUM SPORE 9 [hp_X]/50 mL; STRYCHNOS NUX-VOMICA SEED 3 [hp_X]/50 mL; BERBERIS VULGARIS ROOT BARK 3 [hp_X]/50 mL; CITRULLUS COLOCYNTHIS FRUIT PULP 3 [hp_X]/50 mL; SOLIDAGO VIRGAUREA FLOWERING TOP 3 [hp_X]/50 mL; VERATRUM ALBUM ROOT 3 [hp_X]/50 mL; APIS MELLIFERA 6 [hp_X]/50 mL; TRIBASIC CALCIUM PHOSPHATE 12 [hp_X]/50 mL; SOLANUM DULCAMARA TOP 6 [hp_X]/50 mL; EQUISETUM HYEMALE 4 [hp_X]/50 mL; FERROUS IODIDE 12 [hp_X]/50 mL; FUMARIA OFFICINALIS FLOWERING TOP 4 [hp_X]/50 mL; GENTIANA LUTEA ROOT 5 [hp_X]/50 mL; GERANIUM ROBERTIANUM 4 [hp_X]/50 mL; POTASSIUM IODIDE 8 [hp_X]/50 mL; SODIUM SULFATE 3 [hp_X]/50 mL; PINUS SYLVESTRIS LEAFY TWIG 4 [hp_X]/50 mL; SMILAX ORNATA ROOT 6 [hp_X]/50 mL; SCROPHULARIA NODOSA 3 [hp_X]/50 mL; LOBARIA PULMONARIA 5 [hp_X]/50 mL; TEUCRIUM SCORODONIA FLOWERING TOP 3 [hp_X]/50 mL; VERONICA OFFICINALIS FLOWERING TOP 3 [hp_X]/50 mL
INACTIVE INGREDIENTS: ALCOHOL; WATER; ALCOHOL; WATER; ALCOHOL; WATER

BodyAnew Multipack

ACTIVE INGREDIENTS

BodyAnew Colon & Liver:

Active Ingredients: 30 drops contain:
*Colocynthis 3X 0.3%, *Colocynthis 30X 0.3%, *Colocynthis 200X 0.3%, *Lycopodium clavatum 3X 0.3%, *Lycopodium clavatum 200X 0.3%, *Lycopodium clavatum 1000X 0.3%, *Bryonia 9X 0.22%, Bryonia 29X 0.22%, *Bryonia 3X 0.2%, *Bryonia 15X 0.2%, *Bryonia 200X 0.2%, *Bryonia 1000X 0.2%, *Chelidonium majus 3X 0.2%, *Nux vomica 3X 0.2%, *Nux vomica 10X 0.2%, *Nux vomica 15X 0.2%, *Nux vomica 30X 0.2%, *Nux vomica 200X 0.2%, *Nux vomica 1000X 0.2%, *Colocynthis 9X 0.03%, *Lycopodium clavatum 9X 0.03%,
*Lycopodium clavatum 29X 0.03%, *Bryonia 5X 0.02%

*Natural Ingredients

BodyAnew Kidney:

Active Ingredients: 30 drops contain:
*Berberis vulgaris 3X 10%, *Colocynthis 6X 10%, *Veratrum album 6X 10%, *Colocynthis 3X 3%, *Berberis vulgaris 10X 0.4%, *Berberis vulgaris 30X 0.4%, *Berberis vulgaris 200X 0.4%, *Solidago virgaurea 3X 0.4%, *Solidago virgaurea 10X 0.4%, *Solidago virgaurea 30X 0.4%, *Solidago virgaurea 200X 0.4%, *Colocynthis 30X 0.3%, *Colocynthis 200X 0.3%, *Veratrum album 3X 0.3%, *Veratrum album 30X 0.3%, *Veratrum album 200X 0.3%

*Natural Ingredients

BodyAnew Lymph & Lungs:

Active Ingredients: 30 drops contain:
I*Myosotis arvensis 3X, Natrum sulphuricum 3X, *Scrophularia nodosa 3X, *Teucrium scorodonia 3X, *Veronica officinalis 3X, *Equisetum hyemale 4X, *Fumaria officinalis 4X, *Geranium robertianum 4X, *Nasturtium aquaticum 4X, *Pinus sylvestris 4X, *Gentiana lutea 5X, *Sticta pulmonaria 5X, *Apis mellifica 6X, *Dulcamara 6X, *Sarsaparilla 6X, Kali iodatum 8X, Calcarea phosphorica 12X, Ferrum iodatum 12X, Thyroidinum
12X 5% each

*Natural ingredient

PURPOSE

For the temporary relief of occasional low energy, minor abdominal bloating, upper respiratory symtoms such as cough, runny nose, urinary pain.

KEEP OUT OF REACH OF CHILDREN

BodyAnew Rejuveo:

Keep out of reach of children.

BodyAnew Purity:

Keep out of reach of children.

BodyAnew Fatigue:

Keep out of reach of children.

INDICATIONS AND USAGE

For the temporary relief of occasional low energy, minor abdominal bloating, upper respiratory symtoms such as cough, runny nose, urinary pain.

WARNINGS

If pregnant or breast-feeding, ask a healthcare professsional before use. Keep out of reach of children. Do not use if known hypersensitivity to BodyAnew Colon & Liver™, BodyAnew Kidney™, or BodyAnew Lymph & Lungs™ or any of its ingredients exists. Mild symptoms such as skin outbreaks, and loose stools may occur. Stop and see a doctor if these symtoms persist.

DIRECTIONS

Use for up to 2 weeks. Adults : Add 30 drops or 2 half dropperfuls of each BodyAnew™ formula(Lymph & Lungs, Kidney, Colon & Liver) to water and consume throughtout the day. Do not exceed more than 4 half dropperfuls of each formula per day.perday, taking 10 drops every 4 to 6 hours.

For children under 18 years: Consult your health practitioner.

INACTIVE INGREDIENTS

Organic ethanol, Purified water

PACKAGE LABEL

Add image transcription here...